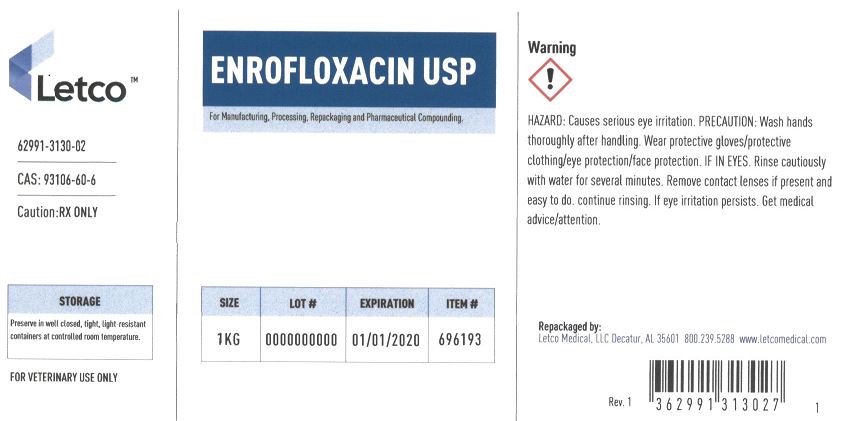 DRUG LABEL: ENROFLOXACIN
NDC: 62991-3130 | Form: POWDER
Manufacturer: LETCO MEDICAL, LLC
Category: other | Type: BULK INGREDIENT - ANIMAL DRUG
Date: 20240718

ACTIVE INGREDIENTS: ENROFLOXACIN 1 g/1 g

ENROFLOXACIN USP

PACKAGE LABEL

Enrofloxacin USP 1kg